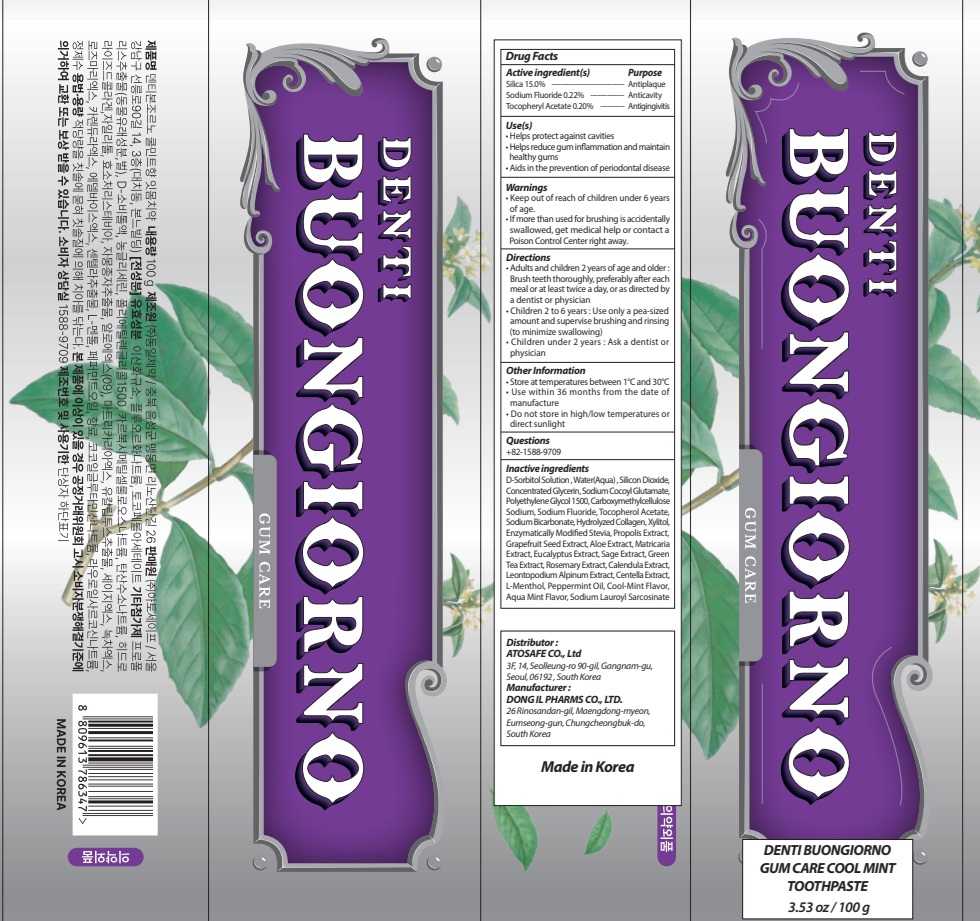 DRUG LABEL: DENTI BUONGIORNO GUM CARE COOL MINT TOOTH
NDC: 73242-1127 | Form: PASTE, DENTIFRICE
Manufacturer: DONG IL PHARMS CO.,LTD
Category: otc | Type: HUMAN OTC DRUG LABEL
Date: 20260116

ACTIVE INGREDIENTS: .ALPHA.-TOCOPHEROL ACETATE 0.2 g/100 g; SODIUM FLUORIDE 0.22 g/100 g; SILICON DIOXIDE 15 g/100 g
INACTIVE INGREDIENTS: SORBITOL; WATER; GLYCERIN

DENTI BUONGIORNO GUM CARE COOL MINT TOOTHPASTE

Active ingredient(s)

Silica 15.0%
Sodium Fluoride 0.22%
Tocopheryl Acetate 0.20%

Purpose

Antiplaque, Anticavity, Antigingivitis

Warnings

• Keep out of reach of children under 6 years of age.
• If more than used for brushing is accidentally swallowed, get medical help or contact a Poison Control Center right away.

KEEP OUT OF REACH OF CHILDREN

Keep out of reach of childrenunder 6 years of age.

INDICATIONS AND USAGE

Use(s)

• Helps remove plaque and tartar buildup
• Helps prevent cavities
• Helps reduce gum inflammation and promote healthy teeth

Directions

• Adults and children 2 years of age and older : Brush teeth thoroughly, preferably after each meal or at least twice a day, or as directed by a dentist or physician

• Children 2 to 6 years : Use only a pea sized amount and supervise child's brushing and rinsing (to minimize swallowing)

• Children under 2 years : Ask a dentist or physician

Other Information

• Store at temperatures between 1°C and 30°C
• Use within 36 months from the date of manufacture
• Do not store in high/low temperatures or direct sunlight

Questions

+82-1588-9709

Inactive ingredients

D-Sorbitol Solution , Water(Aqua) , Silicon Dioxide, Concentrated Glycerin, Sodium Cocoyl Glutamate, Polyethylene Glycol 1500, Carboxymethylcellulose Sodium, Sodium Fluoride, Tocopherol Acetate, Sodium Bicarbonate, Hydrolyzed Collagen, Xylitol, Enzymatically Modified Stevia, Propolis Extract, Grapefruit Seed Extract, Aloe Extract, Matricaria Extract, Eucalyptus Extract, Sage Extract, Green Tea Extract, Rosemary Extract, Calendula Extract, Leontopodium Alpinum Extract, Centella Extract, L-Menthol, Peppermint Oil, Cool-Mint Flavor, Aqua Mint Flavor, Sodium Lauroyl Sarcosinate